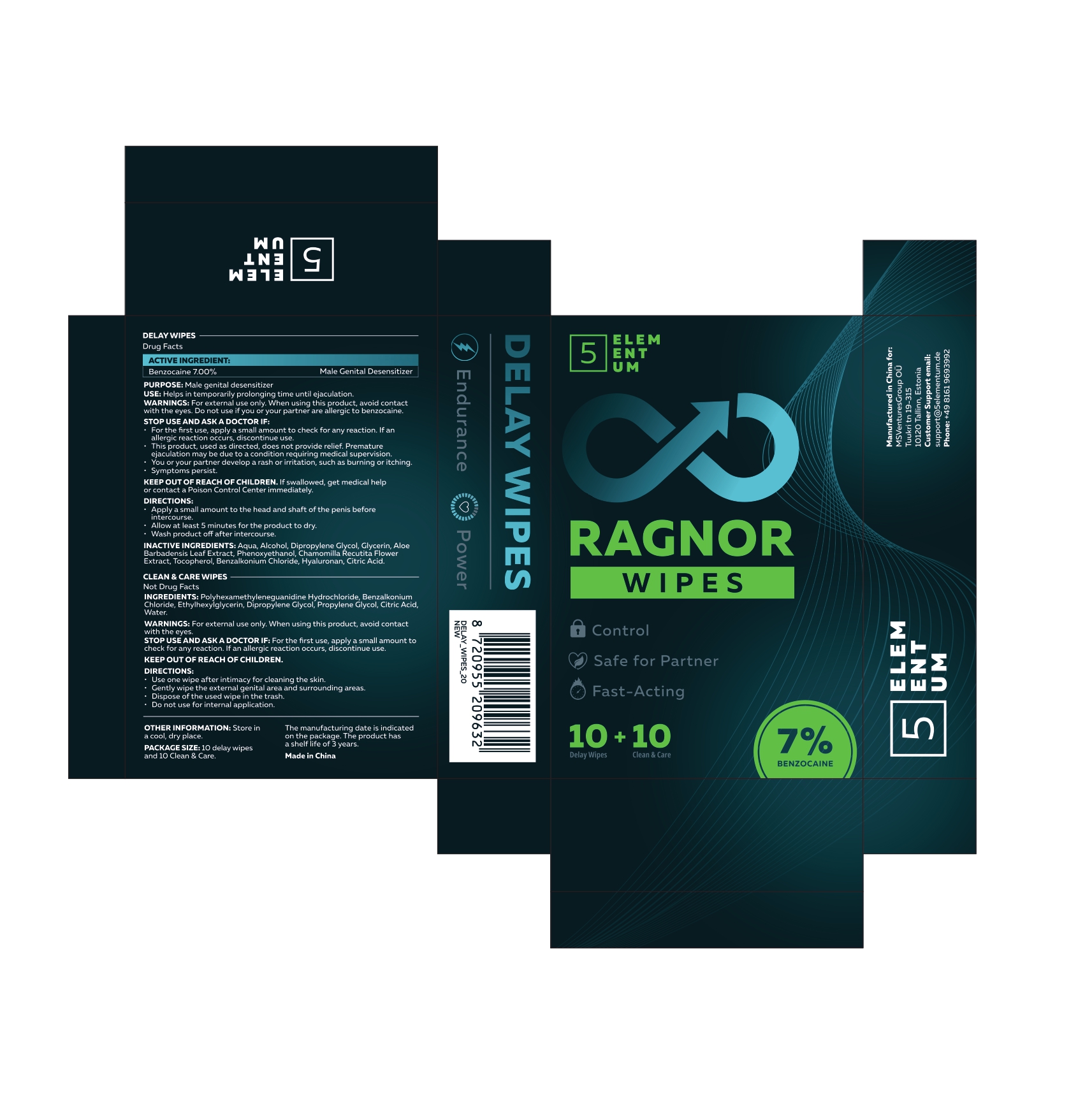 DRUG LABEL: 5 Elementum Delay Wipes
NDC: 87203-001 | Form: CLOTH
Manufacturer: MSVenturesGroup OÜ
Category: otc | Type: HUMAN OTC DRUG LABEL
Date: 20260205

ACTIVE INGREDIENTS: BENZOCAINE 70 mg/1 g
INACTIVE INGREDIENTS: HYALURONIC ACID; ALCOHOL; BENZALKONIUM CHLORIDE; ALOE BARBADENSIS LEAF; ALPHA-TOCOPHEROL; DIPROPYLENE GLYCOL; CITRIC ACID; GLYCERIN; AQUA; PHENOXYETHANOL; MATRICARIA CHAMOMILLA FLOWERING TOP

Outer Package Label Drug Facts

Drug Facts Active Ingredient

Drug Facts

Active ingredient (in each wipe)
Benzocaine 7%

Purpose

Male genital desensitizer

Uses

Helps in reducing oversensitivity of the penile head during intercourse

Warnings Keep out of reach of children.

For external use only. When using this product, avoid contact with eyes.
• This product is intended to be used as directed. Read and follow all directions and warnings provided.
• Stop use and ask a doctor if you or your partner develops rash or irritation.
• If swallowed, get medical help or contact a Poison Control Center right away.
Keep out of reach of children.

Directions

• Apply a small amount to the head and shaft of the penis before intercourse. Allow 5 minutes for the product to dry.
• Wash hands completely after application.

Inactive ingredients

Aqua, Alcohol, Glycereth-26, Glycerin, Aloe Barbadensis Leaf Extract, Chamomilla Recutita Flower Extract, Tocopheryl Acetate, Benzalkonium Chloride, Hyaluronic Acid, Citric Acid.

KEEP OUT OF REACH OF CHILDREN SECTION

Keep out of reach of children.
If swallowed, get medical help or contact a Poison Control Center right away.